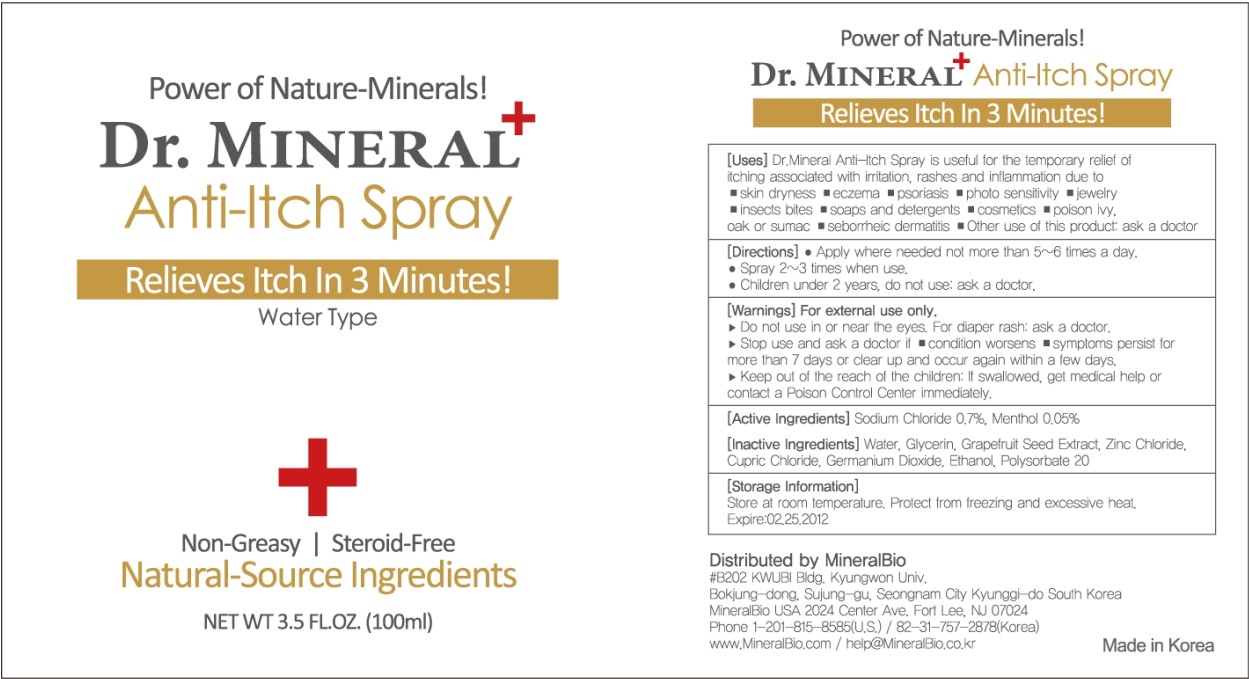 DRUG LABEL: Dr MINERAL Anti-Itch Spray
NDC: 50499-200 | Form: SPRAY
Manufacturer: MineralBio
Category: otc | Type: HUMAN OTC DRUG LABEL
Date: 20100220

ACTIVE INGREDIENTS: SODIUM CHLORIDE 0.7 mL/100 mL; MENTHOL 0.05 mL/100 mL
INACTIVE INGREDIENTS: WATER 98 mL/100 mL; GLYCERIN 0.5 mL/100 mL

[Uses]
Dr. Mineral Anti-Itch Spray is useful for the temporary relief of itching associated with irritation, rashes and inflammation due to
- skin dryness - eczema - psoriasis - photo sensitivity - jewelry - insect bites - soaps and detergents - cosmetics - poison ivy, oak or sumac - seborrheic dermattis - Other use of this product ask a doctor

[Directions]
Apply when needed not more than 5-6 times a day.
- spray 2-3 times when use
- Children under 2 years, do not use: ask a doctor

[Warnings] For external use only.
- Do not use in or near the eyes. For diaper rash: ask a doctor
- Stop use and ask a doctor if
- condition worsens
- symtoms persist for more than 7 days or clear up and occur again within a few days

KEEP OUT OF REACH OF CHILDREN

Keep out of reach of the children. If swallowed, get medical help or contact a Poison Control Center immediately.

ACTIVE INGREDIENT

[Active Ingredients} Sodium Chloride 0.7%, Menthol 0.05%

[Storage]
Store at a room temperature. Protect from freezing and excessive heat.
Expire: 02.25.2012

INACTIVE INGREDIENT

[Inactive Ingredients] Water, Glycerin, Grapefruit Seed Extract, Zinc Chloride, Cupric Chloride, Germanium Dioxide, Ethanol, Polysorbate 20